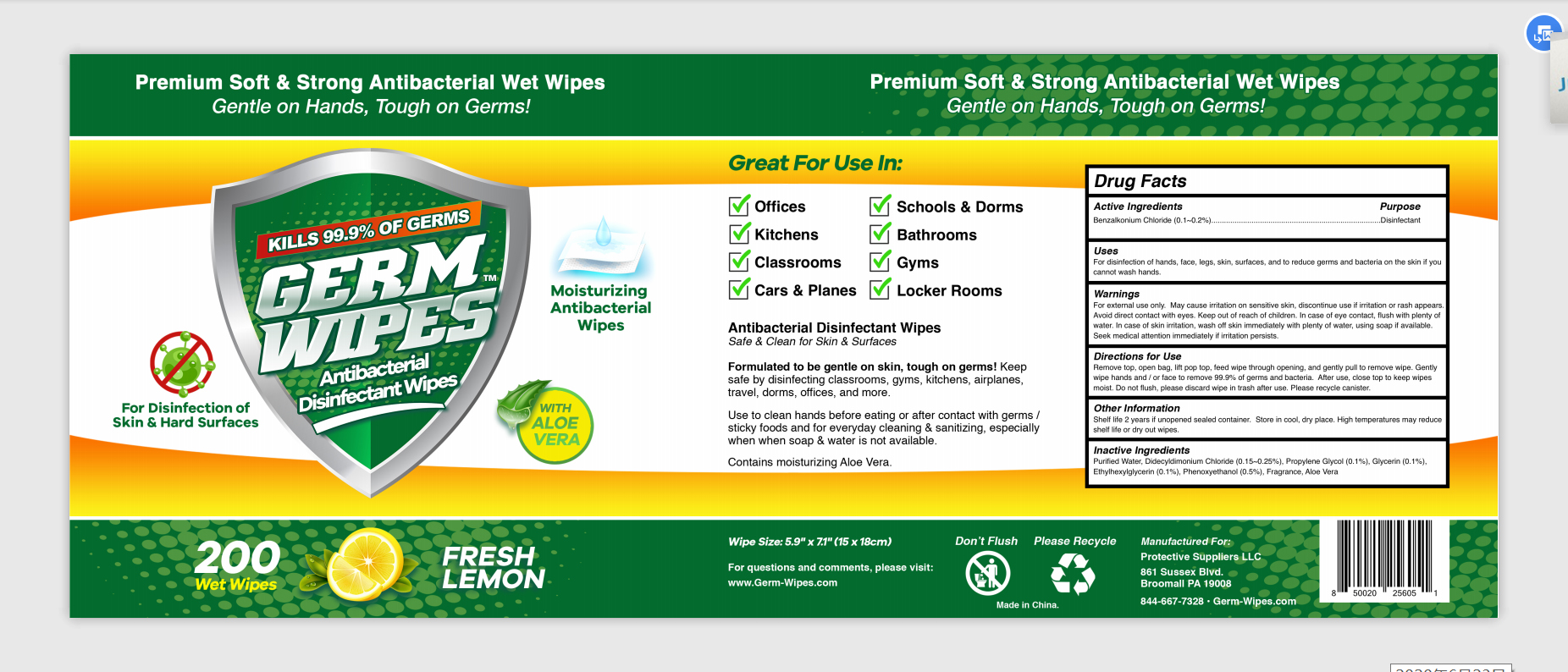 DRUG LABEL: WET WIPES
NDC: 75662-007 | Form: CLOTH
Manufacturer: Ningbo Chenxing Daily Necessities Co., Ltd.
Category: otc | Type: HUMAN OTC DRUG LABEL
Date: 20200701

ACTIVE INGREDIENTS: BENZALKONIUM CHLORIDE 0.1 g/100 g
INACTIVE INGREDIENTS: DIDECYLDIMONIUM CHLORIDE 0.15 g/100 g; ETHYLHEXYLGLYCERIN 0.1 g/100 g; PROPYLENE GLYCOL 0.1 g/100 g; GLYCERIN 0.1 g/100 g; PHENOXYETHANOL 0.5 g/100 g; WATER; ALOE VERA LEAF

WET WIPES

Active Ingredient(s)

Benzalkonium Chloride 0.1%. Purpose: Antiseptic

Purpose

Antiseptic, Wet Wipes

Use

For disinfection of hands, face, legs, skin, surfaces, and to reduce germs and bacteria on the skin if you cannot wash hands

Warnings

For external use only.

DO NOT USE

May cause irritation on sensitive skin, discontinue use if irritation or rash appears. Avoid direct contact with eyes.

WHEN USING

In case of eye contact, flush with plenty of water. In case of skin irritation, wash off skin immediately with plenty of water, using soap if available. Seek medical attention immediately if irritation persists.

Keep out of the reach of children.

Directions

Remove top, open bag, lift pop top, feed wipe through opening, and gently pull to remove wipe. Gently wipe hands and / or face to remove 99.9% of germs and bacteria. After use, close top to keep wipes moist. Do not flush, please discard wipe in trash after use. Please recycle canister.

Other information

Shelf life 2 years if unopened sealed container. Store in cool, dry place. High temperatures may reduce shelf life or dry out wipes

Inactive ingredients

Purified water, Phenoxyethanol, Ethylhexyl Glycerin, Propylene Glycol, Didecyldimonium ChlorideGlycerin, Aloe Vera

Package Label - Principal Display Panel

75662-007-01 200 wipes